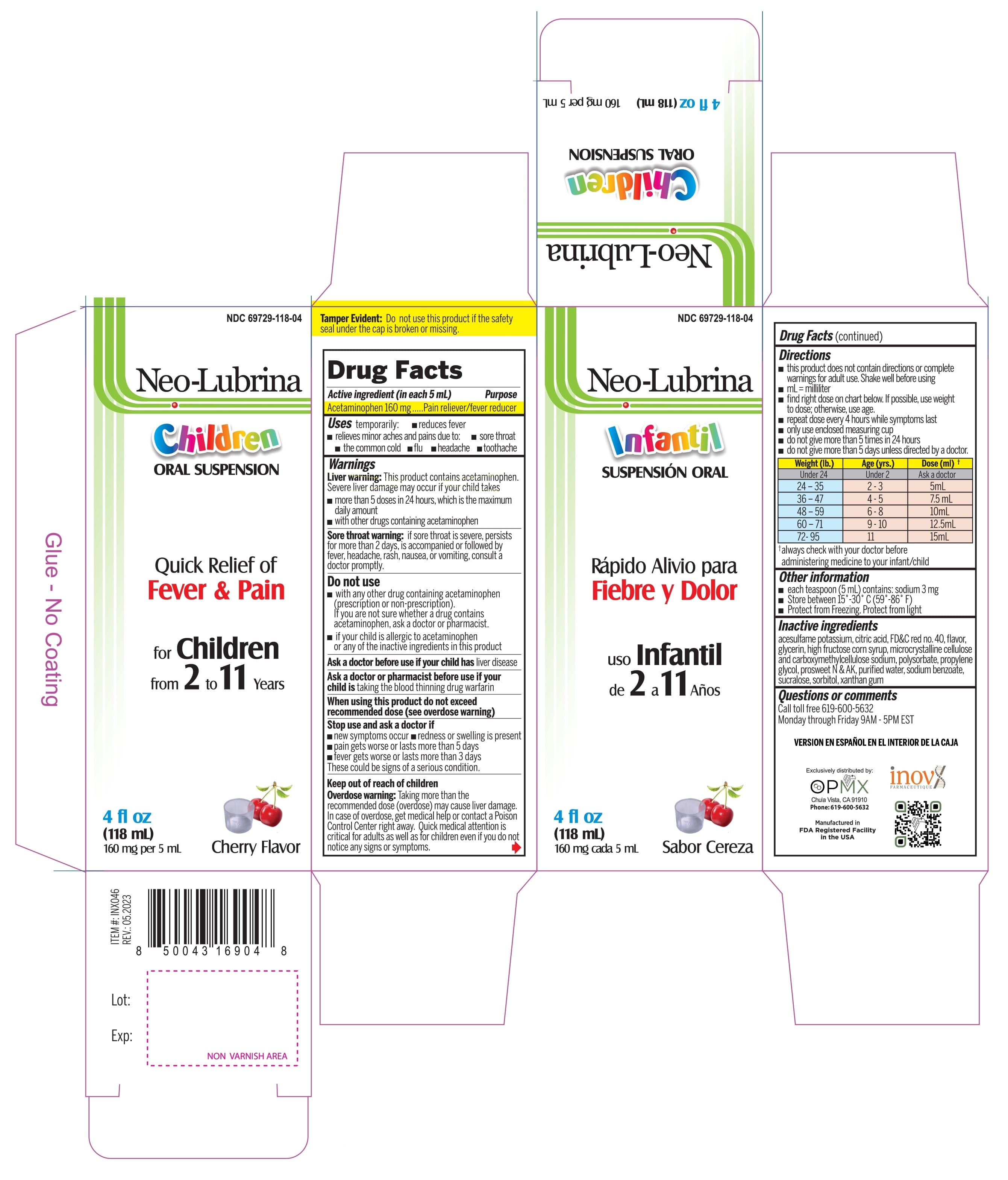 DRUG LABEL: Neo-Lubrina
NDC: 69729-118 | Form: SUSPENSION
Manufacturer: OPMX Chula Vista
Category: otc | Type: HUMAN OTC DRUG LABEL
Date: 20241115

ACTIVE INGREDIENTS: ACETAMINOPHEN 160 mg/5 mL
INACTIVE INGREDIENTS: FD&C RED NO. 40; GLYCERIN; HIGH FRUCTOSE CORN SYRUP; POLYSORBATE 20; PROPYLENE GLYCOL; WATER; SODIUM BENZOATE; SUCRALOSE; SORBITOL; XANTHAN GUM; CARBOXYMETHYLCELLULOSE SODIUM, UNSPECIFIED; ACESULFAME POTASSIUM; MICROCRYSTALLINE CELLULOSE; ANHYDROUS CITRIC ACID

Neo-Lubrina

Active Ingredient(in each 5 mL) Purpose

Acetaminophen 160 mg............. Pain reliever/fever reducer

PURPOSE

Pain Reliever & Fever Reducer

Uses

temporarily:

- reduces fever
- relieves minor aches and pains due to:
- sore throat
- the common cold
- flu
- headache
- toothache

Warnings

Liver warning: This product contains acetaminophen.
Severe liver damage may occur if your child takes takes

- more than 5 doses in 24 hours. which is the maximum daily amount.
- with other drugs containing acetaminophen.

Sore throat warning: if sore throat is severe, persists for more than 2 days, is accompanied or followed by fever, headache, rash, nausea, or vomiting, consult a doctor promptly.

Do not use

- with any other drug containing acetaminophen (prescnption or non-prescription). If you are not sure whether a drug contains acetaminophen, ask a doctor or pharmacist.
- if your child is allergic to acetaminophen or any of the inactive ingredients in this product.

Ask a doctor before use if your child has liver disease.

Ask a doctor or pharmacist before use if your child is taking the blood thinning drug warfarin.

When using this product do not exceed recommened dose (see overdose warning)

Stop use and ask a doctor if

- new sympthoms occur
- redness or swelling is present
- pain gets worse or lasts more than 5 days
- fever gets worse or lasts more than 3 days

These could be signs of a serious condition

Keep out of reach of children.

OVERDOSAGE

Overdose warning: Taking more than the recommended dose (overdose) may cause liver damage. In case of overdose, get medical help or contact a Poison Control Center right away. Quick medical attention is critical for adults as well as for children even if you do not notice any signs or symptoms.

Directions

- this product does not contain directions or complete warnings for adult use. Shake well before using
- mL= millilitar
- find right dose on chart below, if possible, use weight to dose; otherwise, use age
- repeat dose every 4 hours while symptoms last
- only use enclosed measuring syringe
- do not give more than 5 times in 24 hours
- do not give more than 5 days unless directed by a doctor

Weight (lb,) | Age (yrs.) | Dose (mL)*
Under 24 | Under 2 | Ask a doctor
24-35 | 2-3 | 5 mL
36-47 | 4-5 | 7.5 mL
48-59 | 6-8 | 10 mL
60-71 | 9-10 | 12.5 mL
72-95 | 11 | 15 mL

*always check with your doctor before administering medicine to your infant/child

Other information

- Each teaspoon (5 mL) contains: sodium 3 mg
- Store between 15°-30°C (59°-86°F)
- Protect from freezing. Protect from light

Inactive ingredients

acesulfame potassium, citric acid, FD&C red no. 40, flavor, glycerine, high fructose corn syrup, microcrystalline cellulose and carboxymethylcellulose sodium, polysorbate, propylene glycol, prosweet N&AK, purified water, sodium benzoate, sucralose, sorbitol, xanthan gum.

Questions or comments?

Call toll free 619-600-5632
Monday through Fnday 9AM - 5PM EST

PRINCIPAL DISPLAY PANEL

NDC 69729-118-04 Neo-Lubrina